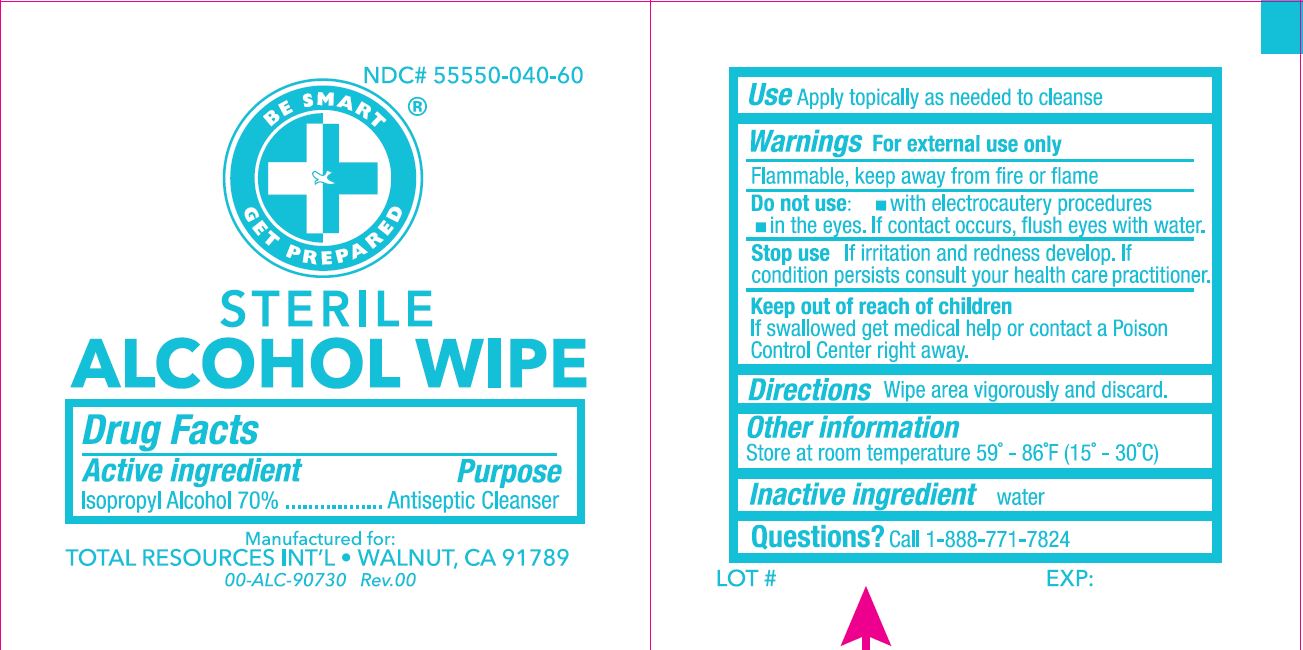 DRUG LABEL: Sterile Alcohol Wipe
NDC: 55550-040 | Form: LIQUID
Manufacturer: Total Resource
Category: otc | Type: HUMAN OTC DRUG LABEL
Date: 20221118

ACTIVE INGREDIENTS: ISOPROPYL ALCOHOL 0.7 mL/1 mL
INACTIVE INGREDIENTS: WATER

TR-1113: NDC# 55550-040-60

Active ingredient

Isopropyl Alcohol 70%

Purpose

Antiseptic Cleanser

Use

Apply topically as needed to cleanse

Warnings

For external use only

Flammable, keep away from fire or flame

Do not use:

- with electrocautery procedures
- in the eyes. If contact occurs, flush eyes with water.

Stop use

If irritation and redness develop. If condition persists consult your health care practitioner.

KEEP OUT OF REACH OF CHILDREN

If swallowed get medical help or contact a Poison Control Center right away.

Directions

Wipe area vigorously and discard.

Other information

Store at room temperature 59° - 86°F (15° - 30°C)

Inactive ingredient

water

Questions?

Call 1-888-771-7824